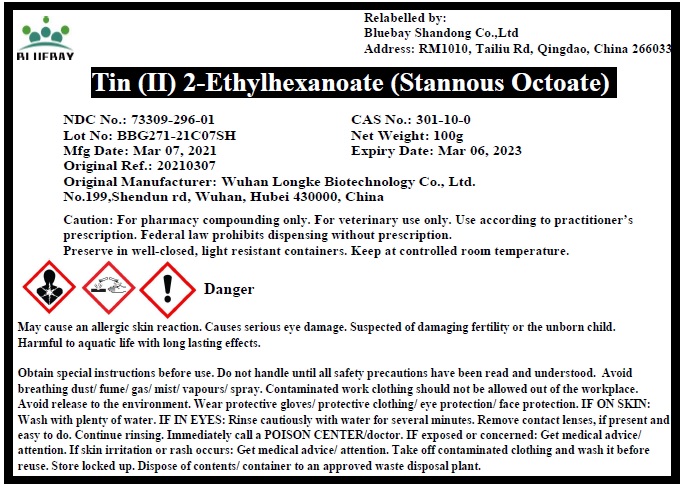 DRUG LABEL: Tin (II) 2-Ethylhexanoate (Stannous Octoate)
NDC: 73309-296 | Form: LIQUID
Manufacturer: BLUEBAY SHANDONG CO.,LTD
Category: other | Type: BULK INGREDIENT
Date: 20210526

ACTIVE INGREDIENTS: STANNOUS 2-ETHYLHEXANOATE 1 g/1 g

Tin (II) 2-Ethylhexanoate (Stannous Octoate)